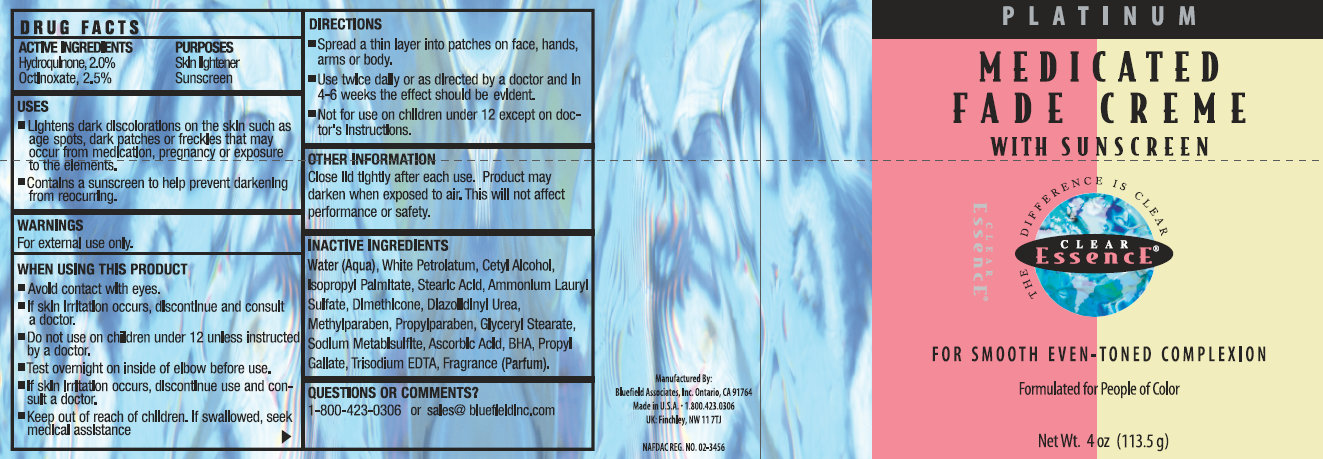 DRUG LABEL: Medicated Fade Creme with Sunscreen
NDC: 16708-002 | Form: CREAM
Manufacturer: Bluefield Associates, Inc.
Category: otc | Type: HUMAN OTC DRUG LABEL
Date: 20151026

ACTIVE INGREDIENTS: HYDROQUINONE 0.02 g/1 g; OCTINOXATE 0.025 g/1 g
INACTIVE INGREDIENTS: ASCORBIC ACID; PROPYL GALLATE; WATER; EDETATE TRISODIUM; GLYCERYL MONOSTEARATE; CETYL ALCOHOL; ISOPROPYL PALMITATE; STEARIC ACID; AMMONIUM LAURYL SULFATE; DIMETHICONE; EDETATE DISODIUM; SODIUM METABISULFITE; BUTYLATED HYDROXYTOLUENE; METHYLPARABEN; PROPYLPARABEN; DIAZOLIDINYL UREA

Medicated Fade Creme with Sunscreen

Active Ingredient

Hydroquinone U.S.P. 2%

Purpose

Skin Lightener

Active Ingredient

Octinoxate 2.5%

Purpose

Sunscreen

Uses:

- Lightens dark discolorations on the skin such as age spots, dark patches or freckles that may occur from medication, pregnancy or exposure to the elements.
- Contains a sunscreen to help prevent darkening from reoccurring.

Warnings

For External use only. Avoid contact with eyes. Some users of this product may experience a mild skin irritation. If skin irritation becomes severe, stop use and consult a doctor.

Do Not use on

children under 12 years of age unless directed by a doctor.

Keep out of the reach of children.

If swallowed, get medical help or contact a Poison Control Center right away. If pregnant or breast-feeding, ask a doctor before use.

Questions or Comments?

1-800-423-0306 or sales@bluefieldInc.com

Directions

- Spread a thin layer into patches on face, hands, arms or body..
- Use twice daily or as directed by a doctor and in 4-6 weeks the effect should be evident.
- Not for use on children under 12 except on doctor's intructions.

Inactive Ingredients

Water (Aqua), White Petrolatum, Cetyl Alcohol, Isopropyl Palmitate, Stearic Acid, Propylene Glycol, Stearic Acid, Ammonium Lauryl Sulfate, Dimethicone, Diazolidinyl Urea, Methylparaben, Propylparaben, Glyceryl Stearate,Sodium Metabisulfite, Ascorbic Acid, BHA, Propul Gallate,Trisodium EDTA, Fragrance (Parfum).